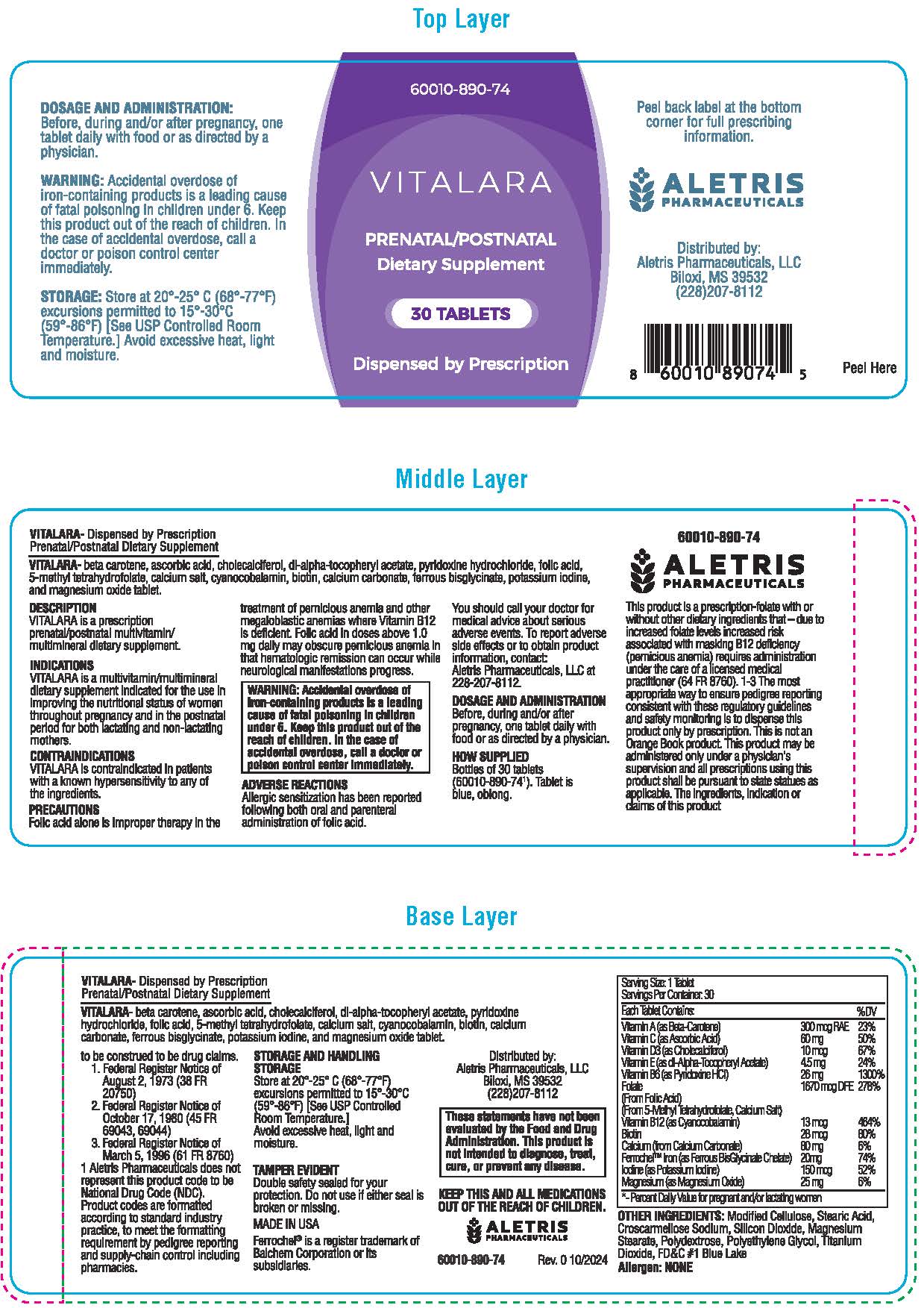 DRUG LABEL: VITALARA
NDC: 86001089074 | Form: TABLET
Manufacturer: Aletris Pharmaceuticals, LLC
Category: other | Type: DIETARY SUPPLEMENT
Date: 20241229

ACTIVE INGREDIENTS: ASCORBIC ACID 60 mg/1 1; BETA CAROTENE 300 ug/1 1; CHOLECALCIFEROL 10 ug/1 1; .ALPHA.-TOCOPHEROL ACETATE, DL- 45 mg/1 1; PYRIDOXINE HCL 26 mg/1 1; FOLIC ACID 1670 ug/1 1; CYANOCOBALAMIN 13 ug/1 1; BIOTIN 28 ug/1 1; CALCIUM CARBONATE 80 mg/1 1; FERROUS BISGLYCINATE 20 mg/1 1; POTASSIUM IODIDE 150 ug/1 1; MAGNESIUM OXIDE 25 mg/1 1
INACTIVE INGREDIENTS: HYDROXYPROPYL CELLULOSE, UNSPECIFIED; STEARIC ACID; CROSCARMELLOSE SODIUM; SILICON DIOXIDE; MAGNESIUM STEARATE; TITANIUM DIOXIDE; POLYETHYLENE GLYCOL, UNSPECIFIED; POLYDEXTROSE; FD&C BLUE NO. 1

VITALARA
PRENATAL/POSTNATAL
Dietary Supplement

HEALTH CLAIM

VITALARA-Dispensed by Prescription

STATEMENT OF IDENTITY

VITALARA- beta carotene, ascorbic acid, cholecalciferol, dl-alpha-tocopheryl acetate, pyridoxine hydrochloride, folic acid, 5-methyl tetrahydrofolate, calcium salt, cyanocobalamin, biotin, calcium carbonate, ferrous bisglycinate, potassium iodine, and magnesium oxide tablet.

Serving Size: 1 Tablet; Servings Per Container: 30
Each Tablet Contains: |  | %DV
Vitamin A (as Beta-Carotene) | 300 mcg RAE | 23%
Vitamin C (as ascorbic acid) | 60 mg | 50%
Vitamin D3 (as cholecalciferol) | 10 mcg | 67%
Vitamin E (as dl-Alpha-Tocopheryl Acetate) | 45 mg | 24%
Vitamin B6 (as pyridoxine HCl) | 26 mg | 1300%
Folate; (From Folic Acid); (From 5-Methyl Tetrahydrofolate, Calcium Salt) | 1670 mcg DFE | 278%
Vitamin B12 (as Cyanocobalamine) | 13 mcg | 464%
Biotin | 28 mg | 80%
Calcium (from Calcium Carbonate) | 80 mg | 6%
FerrochelTM Iron (as ferrous BisGlycinate Chelate) | 12 mg | 44%
Iodine (as potassium iodide) | 150 mcg | 52%
Magnesium (as Magnesium oxide) | 25 mg | 6%
* -Percent Daily Value for pregnant and/or lactating women

OTHER INGREDIENTS: Modified Cellulose, Stearic Acid, Croscarmellose Sodium, Silicon Dioxide, Magnesium Stearate, Polyethylene Glycol, Polydextrose, Titanium Dioxide, FD&C #1 Blue Lake

Allergen: NONE

DESCRIPTION

VITALARA is a prescription prenatal/postnatal multivitamin/ multimineral dietary supplement.

INDICATIONS

VITALARA is a multivitamin/multimineral dietary supplement indicated for the use in improving the nutritional status of women throughout pregnancy and in the postnatal period for both lactating and non-lactating mothers.

CONTRADINDICATIONS

VITALARA is contraindicated in patients with a known hypersensitivity to any of the ingredients.

WARNING

Accidental overdose of iron-containing products is a leading cause of fatal poisoning in children under 6. Keep this product out of the reach of children. In the case of accidental overdose, call a doctor or poison control center immediately.

ADVERSE REACTIONS

Allergic sensitization has been reported following both oral and parenteral administration of folic acid.

You should call your doctor for medical advice about serious adverse events. To report adverse side effects or to obtain product information, contact: Aletris Pharmaceuticals, LLC at 228-207-8112.

DOSAGE AND ADMINISTRATION

Before, during and/or after pregnancy, one tablet daily with food or as directed by a physician.

PRECAUTION:

Folic acid alone is improper therapy in the treatment of pernicious anemia and other megaloblastic anemias where Vitamin B12 is deficient. Folic acid in doses above 1.0 mg daily may obscure pernicious anemia in that hematologic remission can occur while neurological manifestations progress.

STORAGE

Store at 20°-25°C (68°-77°F) excursions permitted to 15°-30°C (59°-86°F) [See USP Controlled Room Temperature.] Avoid excessive heat, light
and moisture.